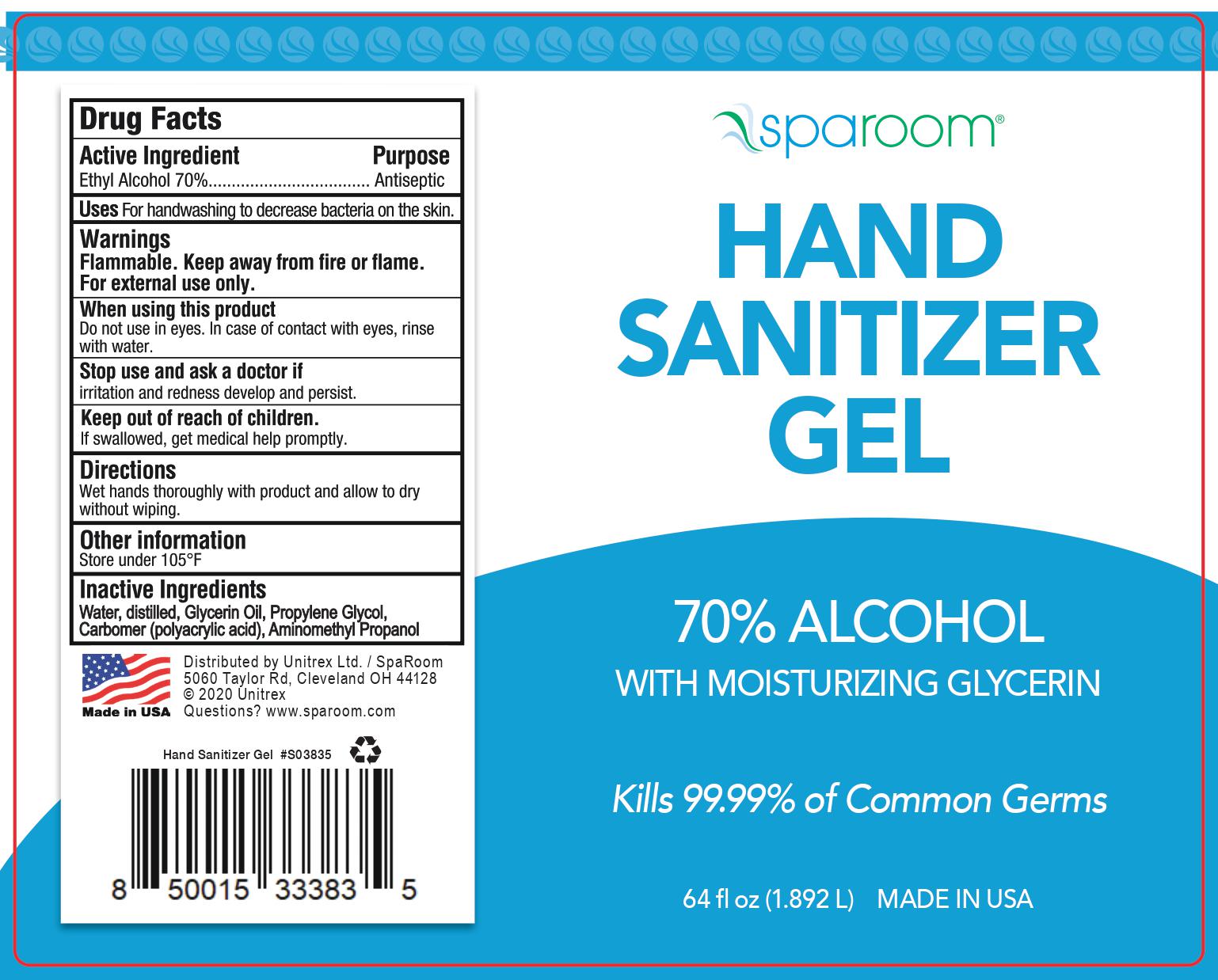 DRUG LABEL: Unscented Hand Sanitizer Gel
NDC: 73769-050 | Form: GEL
Manufacturer: NATURE'S FUSIONS, LLC
Category: otc | Type: HUMAN OTC DRUG LABEL
Date: 20240801

ACTIVE INGREDIENTS: ALCOHOL 69.8 mL/100 mL
INACTIVE INGREDIENTS: WATER; PROPYLENE GLYCOL; AMINOMETHYLPROPANOL; CARBOMER HOMOPOLYMER, UNSPECIFIED TYPE; GLYCERIN

Hand Sanitizer Gel - Sparoom

DOSAGE AND ADMINISTRATION

Uses: For handwashing to decrease bacteria on the skin.

WARNINGS

Flammable. Keep away from fire or flame.

For external use only.

When using this product

Do not use in eyes. In case of contact with eyes, rinse with water.

Stop use and ask a doctor if

irritation and redness develope and persist.

INACTIVE INGREDIENT

Water, distilled, Glycerin Oil, Propylene Glycol. Carbomer (Polyacrylic acid), aminomethyl propanol

INDICATIONS AND USAGE

Uses: For handwashing to decrease bacteria on the skin.

Keep out of reach of children.

If swallowed, get medical help promptly.

PURPOSE

Antiseptic

ACTIVE INGREDIENT

Ethyl Alcohol 70% ... Antiseptic

Other Information

Store under 105º F

PACKAGE LABEL

Unscented Sanitizer Gel